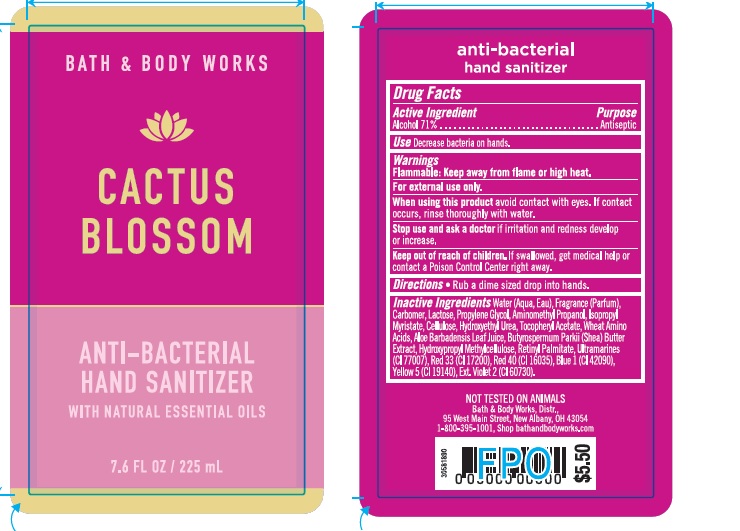 DRUG LABEL: Anti-Bacterial Hand Sanitizer
NDC: 62670-6195 | Form: GEL
Manufacturer: Bath & Body Works, Inc.
Category: otc | Type: HUMAN OTC DRUG LABEL
Date: 20211215

ACTIVE INGREDIENTS: ALCOHOL 68 mL/100 mL
INACTIVE INGREDIENTS: WATER

ACTIVE INGREDIENT

Alcohol 71%

PURPOSE

Antiseptic

USE

Decrease bacteria on hands.

WARNINGS

For external use only.

FLAMMABLE

Keep away from flame or high heat.

WHEN USING THIS PRODUCT

avoid contact with eyes. If contact occurs, rinse thoroughly with water.

STOP USE AND ASK A DOCTOR

if irritation and redness develop or increase.

KEEP OUT OF REACH OF CHILDREN

If swallowed, get medical help or contact a Poison Control Center right away.

DIRECTIONS

- Rub a dime sized drop into hands.

INACTIVE INGREDIENTS

Water (Aqua, Eau), Fragrance (Parfum), Carbomer, Lactose, Propylene Glycol, Aminomethyl Propanol, Isopropyl Myristate, Cellulose, Hydroxyethyl Urea, Tocopheryl Acetate, Wheat Amino Acids, Aloe Barbadensis Leaf Juice, Butyrospermum Parkii (Shea) Butter Extract, Hydroxypropyl Methylcellulose, Retinyl Palmitate, Ultramarines (CI 77007), Red 33 (CI 17200), Red 40 (CI 16035), Blue 1 (CI 42090), Yellow 5 (CI 19140), Ext. Violet 2 (CI 60730).

COMPANY INFORMATION

Bath & Body Works, Distr.

Reynoldsburg, Ohio 43068

1-800-395-1001

www.bathandbodyworks.com